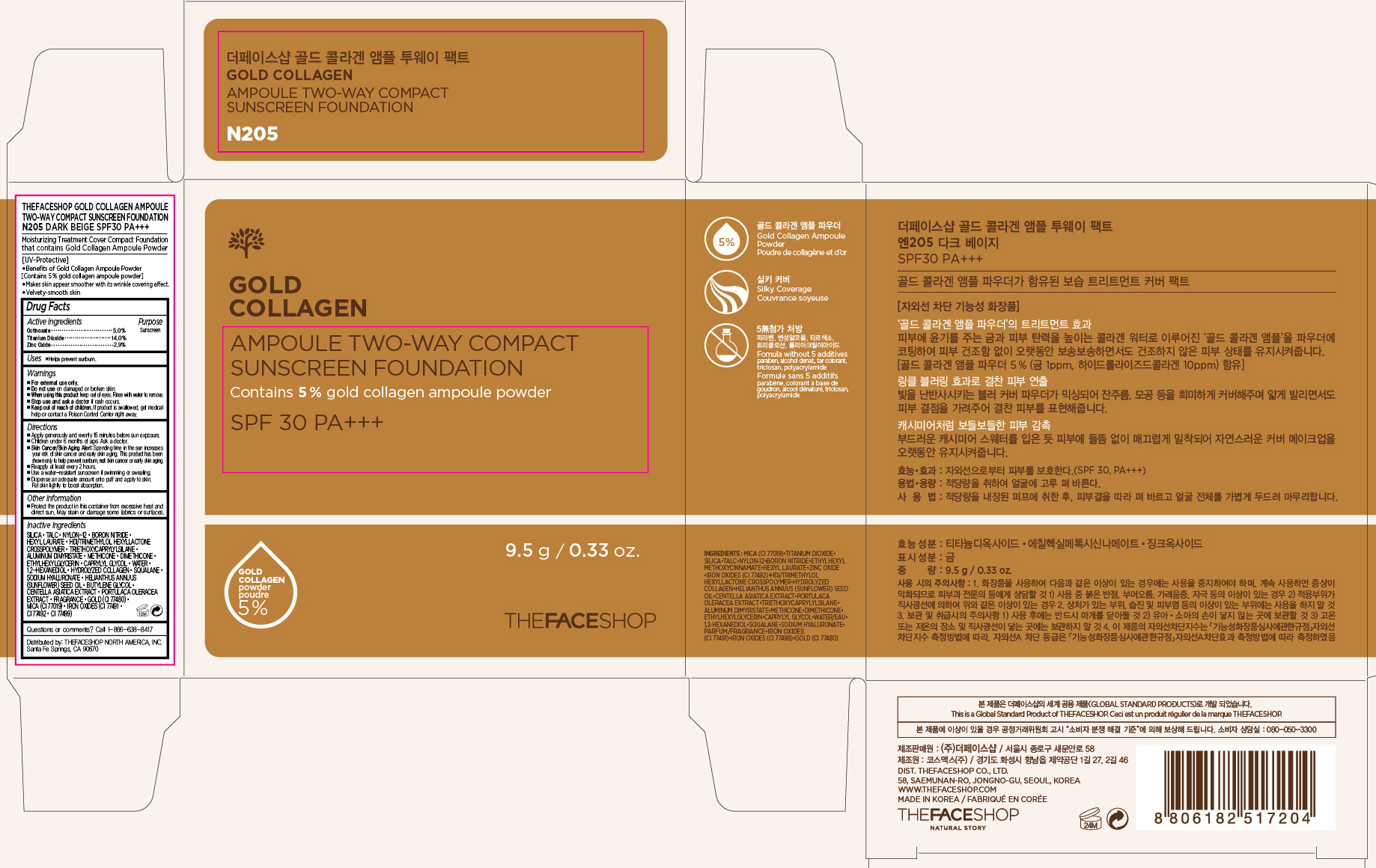 DRUG LABEL: GOLD COLLAGEN
NDC: 51523-466 | Form: CREAM
Manufacturer: THEFACESHOP CO., LTD.
Category: otc | Type: HUMAN OTC DRUG LABEL
Date: 20150928

ACTIVE INGREDIENTS: OCTINOXATE 0.48 g/9.5 g; TITANIUM DIOXIDE 1.33 g/9.5 g; ZINC OXIDE 0.28 g/9.5 g
INACTIVE INGREDIENTS: WATER

GOLD COLLAGEN AMPOULE TWO-WAY COMPACT SUNSCREEN FOUNDATION N205 DARK BEIGE SPF30 PA 34200466

Active Ingredients:

Octinoxate 5.0 %
Titanium Dioxide 14.0 %
Zinc Oxide 2.9 %

Purpose

Sunscreen
Sunscreen
Sunscreen

Uses:

Helps prevent sunburn.

Warnings:

For external use only.

Do not use on damaged or broken skin

When using this product keep out of eyes. Rinse with water to remove.

Stop use and ask a doctor if rash occurs.

Keep out of reach of children. If product is swallowed, get medical help or contact a Poison Control Center right away.

Directions

Apply generously and evenly 15 minutes before sun exposure.
Children under 6 months of age: Ask a doctor.
Skin Cancer/Skin Aging Alert: Spending time in the sun increases your risk of skin cancer and early skin aging. This product has been shown only to help prevent sunburn, not skin cancer or early skin aging.
Reapply at least every 2 hours.
Use a water-resistant sunscreen if swimming or sweating.

Dispense an adequate amount onto the puff and apply to skin. Pat skin lightly to boost absorption.

OTHER SAFETY INFORMATION

Protect the product in this container from excessive heat and direct sun.

May stain or damage some fabrics or surfaces.

INACTIVE INGREDIENT

Silica, Talc, Nylon-12, Boron Nitride, Hexyl Laurate, HDI/Trimethylol Hexyllactone Crosspolymer, Triethoxycaprylylsilane, Aluminum Dimyristate, Methicone, Dimethicone, Ethylhexylglycerin, Caprylyl Glycol, Water, 1,2-Hexanediol, Hydrolyzed Collagen, Squalane, Sodium Hyaluronate, Helianthus Annuus (Sunflower) Seed Oil, Butylene Glycol, Centella Asiatica Extract, Portulaca Oleracea Extract, Fragrance, Gold (CI 77480), Mica (CI 77019), Iron Oxides (CI 77491, CI 77492, CI 77499)

Questions or comments? Call 1-866-638-8417

Distributed by:

THEFACESHOP NORTH AMERICA, INC.

Santa Fe Springs, CA 90670

PACKAGE LABEL

GOLD COLLAGEN

AMPOULE TWO-WAY COMPACT SUNSCREEN FOUNDATION

N205 DARK BEIGE SPF30 PA+++